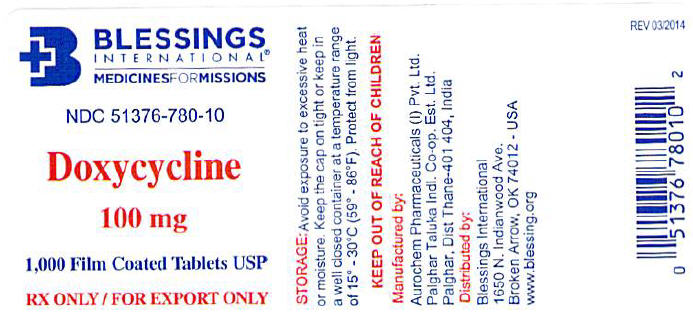 DRUG LABEL: Doxycycline
NDC: 51376-780 | Form: TABLET, FILM COATED
Manufacturer: Blessings International
Category: prescription | Type: HUMAN PRESCRIPTION DRUG LABEL
Date: 20200122

ACTIVE INGREDIENTS: Doxycycline 100 mg/1 1
INACTIVE INGREDIENTS: Magnesium Stearate; Isopropyl Alcohol; Methylene Chloride; Microcrystalline Cellulose; Talc; Starch, Potato

Doxycycline

PRINCIPAL DISPLAY PANEL - 100 mg Tablet Bottle Label

BLESSINGS
INTERNATIONAL®
MEDICINESFORMISSIONS

NDC 51376-780-10

Doxycycline

100 mg

1,000 Film Coated Tablets USP

RX ONLY / FOR EXPORT ONLY